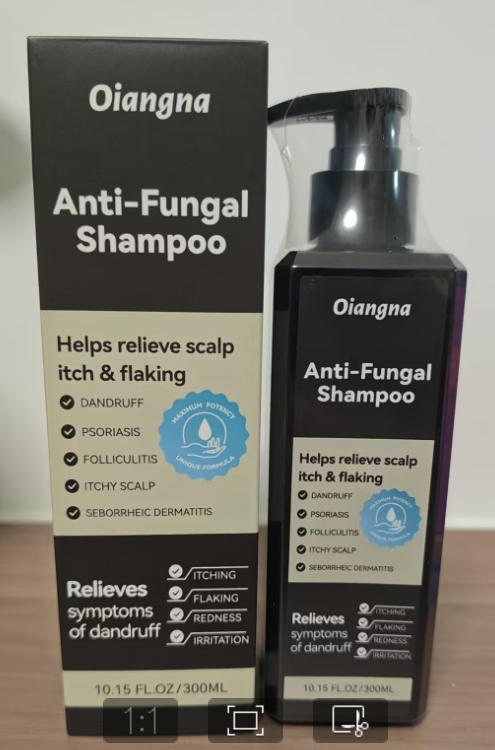 DRUG LABEL: Oiangna Anti Fungal
NDC: 87204-195 | Form: SHAMPOO
Manufacturer: Guangzhou Huixue Biotechnology Co., Ltd.
Category: otc | Type: HUMAN OTC DRUG LABEL
Date: 20251222

ACTIVE INGREDIENTS: SALICYLIC ACID 2 mg/300 mL; SELENIUM SULFIDE 1 mg/300 mL
INACTIVE INGREDIENTS: AQUA; COCAMIDOPROPYL BETAINE; SODIUM CHLORIDE; ETHYLHEXYLGLYCERIN; MACADAMIA TERNIFOLIA SEED OIL; HEXAMIDINE DIISETHIONATE; PHENOXYETHANOL; CITRIC ACID; SODIUM LAUROYL GLUTAMATE; CETEARYL ALCOHOL; COCAMIDOPROPYLAMINE OXIDE; ALOE BARBADENSIS LEAF JUICE

ACTIVE INGREDIENT

Salicylic Acid 2%
Selenium sulfide 1%

INACTIVE INGREDIENT

Water (Aqua), Sodium Lauroyl Glutamate, Cocamidopropyl Betaine, Cetearyl Alcohol, Cocamidopropylamine Oxide, Sodium Chloride, PPG-3 Caprylyl Ether, Polyquaternium-10, Polyquaternium-47, Disodium EDTA, Citric Acid, Propylene Glycol, Sodium Cocamidopropyl PG-Dimonium Chloride Phosphate, Hexamidine Diisethionate, Phenoxyethanol, Ethylhexylglycerin, Aloe Barbadensis Leaf Juice, Rosmarinus Officinalis (Rosemary) Leaf Oil, Melaleuca Alternifolia(Tea Tree) Leaf Oil, Macadamia Ternifolia Seed Oil, Hydrolyzed Corn Starch, Coptis Chinensis Root Extract, Houttuynia Cordata Extract, Panax Ginseng Root Extract, Nymphaea Alba Flower Extract

PURPOSE

Antibacterial shampoo

INDICATIONS AND USAGE

Helps reduce dandruff and control flaking Helps soothe scalp itching and irritation Helps restore scalp comfort and balance ·Leaves hair feeling fresh, clean, and healthy

WARNINGS

Warnings For external use only. Avoid contact with eyes. if contact occurs, rinse thoroughly with water. Stop use and ask a doctor if condition worsens or does not improve after regular use. Keep out of reach of children. If swallowed, get medical help or contact a Poison Control Center right away

KEEP OUT OF REACH OF CHILDREN

If swallowed, get medical help or contact a Poison Control Center right away.

WHEN USING

1. Do not apply on other parts of the body, For topical use only on the scalp
2. Avoid contact with the eyes in case of accidental contact rinse eyes with large arnounts of cool tap water.

DO NOT USE

You have no family history of hair loss,hair loss is sudden and/or patchy
You do not know the reason for you hair loss.
You ae under 18 years of age, Do not use it on babies and children your scalp is red.inflamed.infected, irritated, or painful
You use other medicines on the scalp.Ask a doctor before use if you hace heart disease.

STOP USE

Chest pain, rapid heart beat, faintness, or dizziness occurs sudden, unexplained weight gain occurs,your hands or feet swell.

DOSAGE AND ADMINISTRATION

Apply a small amount to wet hair and scalp. Gently massage into lather, leave on for 2-3 minutes. Rinse thoroughly. • Use 2-3 times per week or as needed.